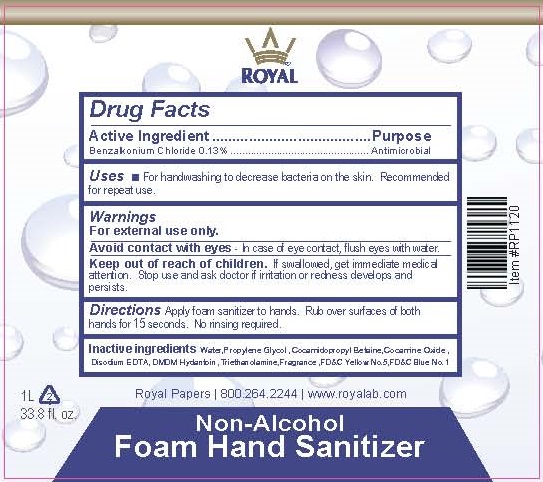 DRUG LABEL: Royal Non-Alcohol Foam Hand Sanitizer
NDC: 70415-205 | Form: SOLUTION
Manufacturer: CWGC LA Inc.
Category: otc | Type: HUMAN OTC DRUG LABEL
Date: 20230921

ACTIVE INGREDIENTS: BENZALKONIUM CHLORIDE 0.13 g/100 mL
INACTIVE INGREDIENTS: WATER; PROPYLENE GLYCOL; COCAMIDOPROPYL BETAINE; COCAMINE OXIDE; EDETATE DISODIUM; DMDM HYDANTOIN; TROLAMINE; FD&C YELLOW NO. 5; FD&C BLUE NO. 1

CWGC (as PLD) - Royal Non-Alcohol Foam Hand Sanitizer (70415-205)

Active ingredient

BENZALKONIUM CHLORIDE 0.13%

Purpose

Antibacterial

Uses

- For handwashing to reduce bacteria on the skin. Recommended for repeated use.

Warnings

For external use only

Avoid contact with eyes. In case of eye contact, flush eyes with water.

Keep out of reach of children.

If swallowed, get medical help or contact a Poison Control Center right away.

Stop use and ask a doctor if irritation or redness develops and persists.

Directions

- Apply foam sanitizer to hands.
- Rub over surfaces of both hands for 15 seconds.
- No rinsing required.

Inactive ingredients

Water, Coco-Glucoside, Laurtrimonium Chloride, Cocamidopropylamine Oxide, Citric Acid, Fragrance.